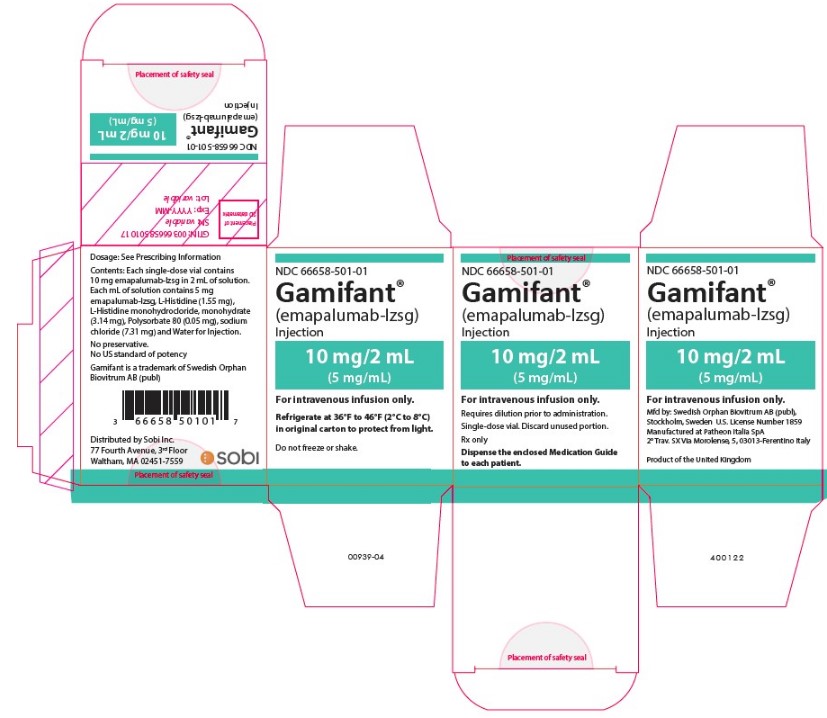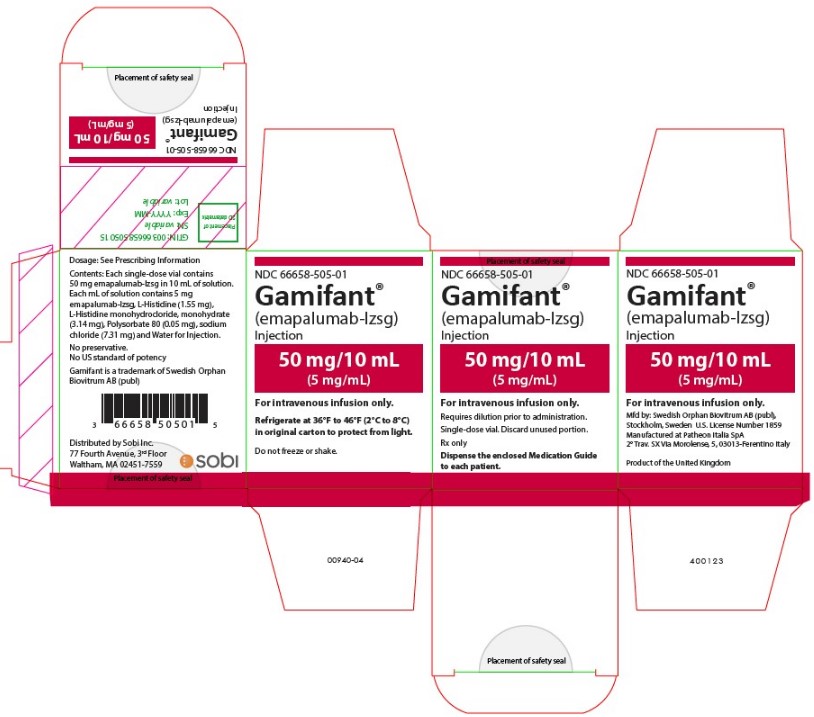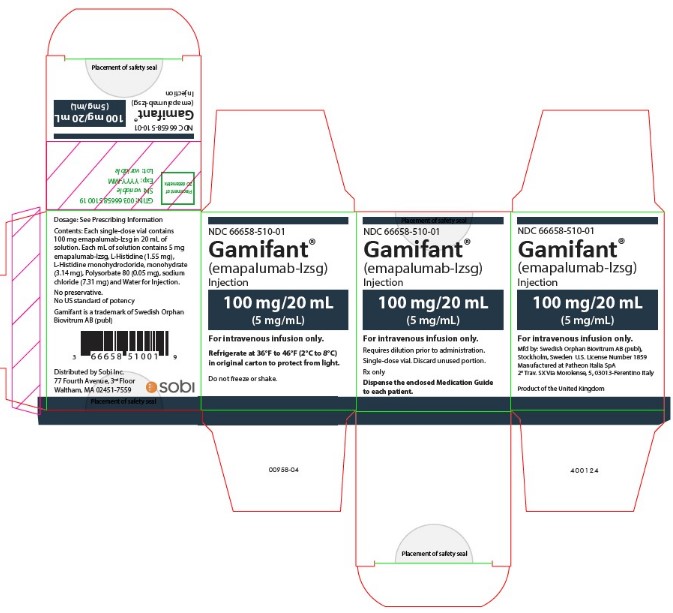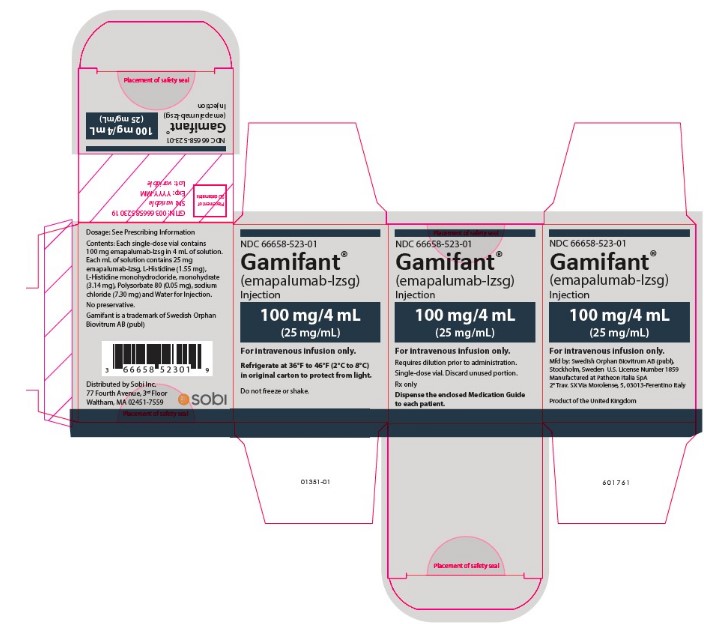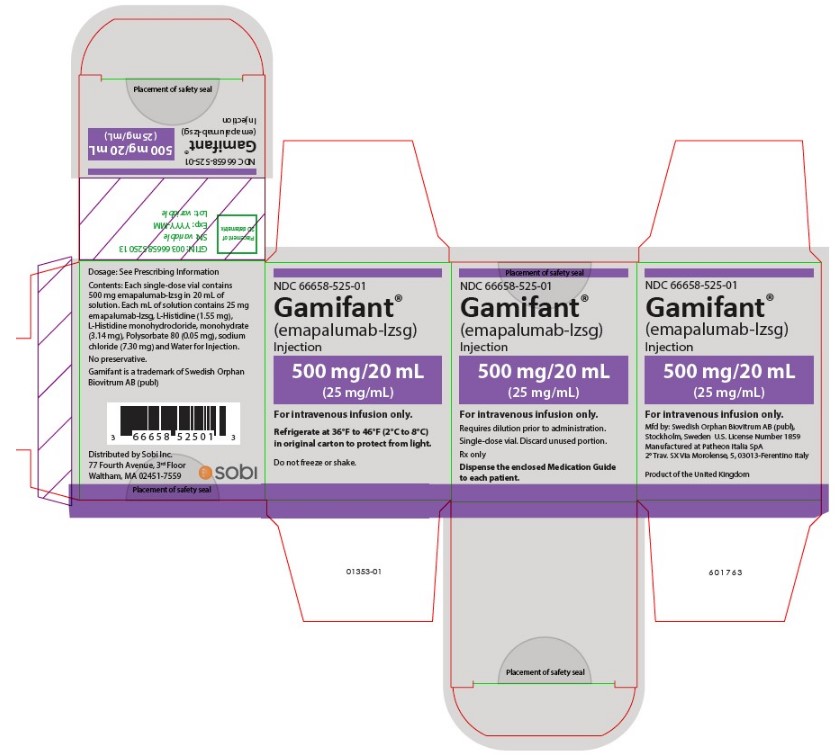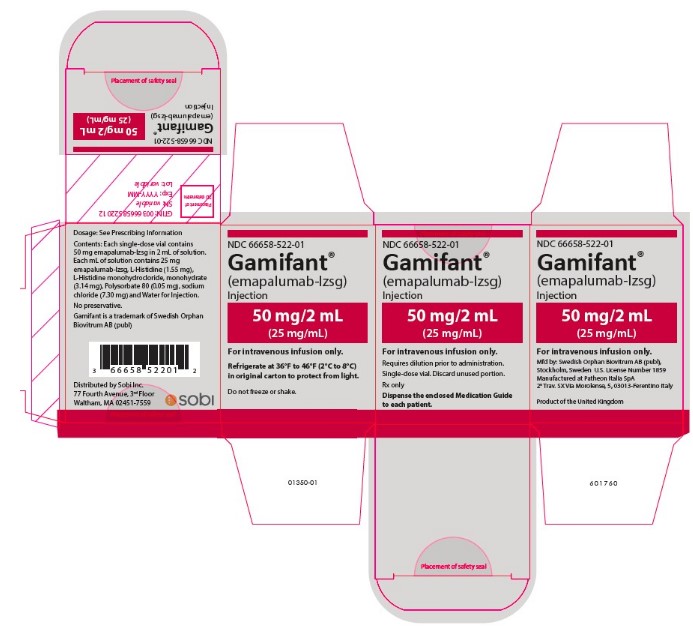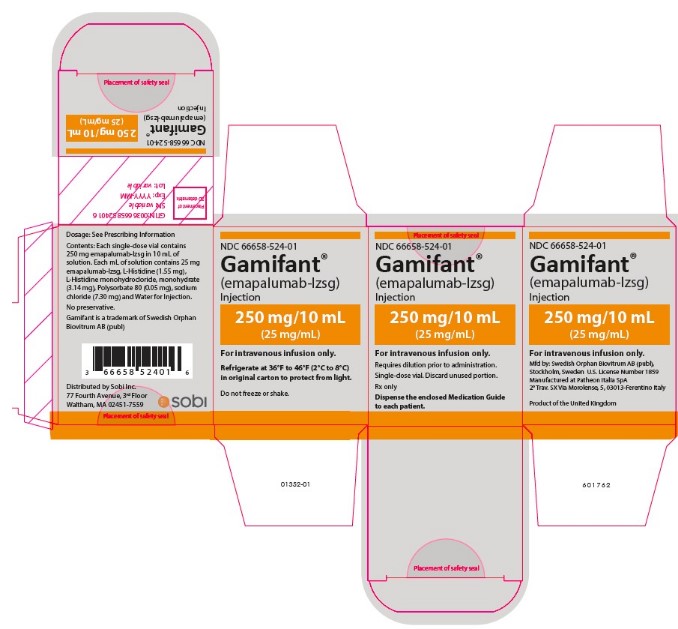 DRUG LABEL: GAMIFANT
NDC: 66658-501 | Form: INJECTION
Manufacturer: Swedish Orphan Biovitrum AB (publ)
Category: prescription | Type: HUMAN PRESCRIPTION DRUG LABEL
Date: 20250630

ACTIVE INGREDIENTS: EMAPALUMAB 10 mg/2 mL
INACTIVE INGREDIENTS: HISTIDINE MONOHYDROCHLORIDE MONOHYDRATE; POLYSORBATE 80; SODIUM CHLORIDE; WATER; HISTIDINE

HIGHLIGHTS OF PRESCRIBING INFORMATION

These highlights do not include all the information needed to use GAMIFANT safely and effectively. See full prescribing information for GAMIFANT.
GAMIFANT® (emapalumab-lzsg) injection, for intravenous use
Initial U.S. Approval: 2018

RECENT MAJOR CHANGES

Indications and Usage (1) 6/2025
Dosage and Administration (2.2, 2.3) 6/2025
Warnings and Precautions (5.1, 5.3) 6/2025

1 INDICATIONS AND USAGE

GAMIFANT is an interferon gamma (IFNγ) neutralizing antibody indicated for the treatment of:

- adult and pediatric (newborn and older) patients with primary hemophagocytic lymphohistiocytosis (HLH) with refractory, recurrent or progressive disease or intolerance with conventional HLH therapy. (1)
- adult and pediatric (newborn and older) patients with HLH/macrophage activation syndrome (MAS) in known or suspected Still’s disease, including systemic Juvenile Idiopathic Arthritis (sJIA), with an inadequate response or intolerance to glucocorticoids, or with recurrent MAS. (1)

2 DOSAGE AND ADMINISTRATION

For intravenous infusion only:

- Primary HLH recommended starting dosage: 1 mg/kg as an intravenous infusion over 1 hour twice per week. (2.1)
- HLH/MAS in Still’s disease recommended starting dose: 6 mg/kg, followed by 3 mg/kg every 3 days for 5 doses, then 3 mg/kg twice per week. Given as an intravenous infusion over 1 hour. (2.2)
- For both indications, the dose may be titrated up to a maximum of 10 mg/kg. (2.5, 2.6)

3 DOSAGE FORMS AND STRENGTHS

Injection:

• 10 mg/2 mL (5 mg/mL) solution in a single-dose vial (3)

• 50 mg/10 mL (5 mg/mL) solution in a single-dose vial (3)

• 100 mg/20 mL (5 mg/mL) solution in a single-dose vial (3)

• 50 mg/2 mL (25 mg/mL) solution in a single-dose vial (3)

• 100 mg/4 mL (25 mg/mL) solution in a single-dose vial (3)

• 250 mg/10 mL (25 mg/mL) solution in a single-dose vial (3)

• 500 mg/20 mL (25 mg/mL) solution in a single-dose vial (3)

4 CONTRAINDICATIONS

- None. (4)

5 WARNINGS AND PRECAUTIONS

- Infections: Monitor patients for signs and symptoms and treat promptly. Test for latent tuberculosis. Consider administering prophylactic treatment against Herpes Zoster, Pneumocystis jirovecii and fungal infections. (5.1)
- Live Vaccines: Do not administer live or live attenuated vaccines to patients receiving GAMIFANT. (5.2)
- Infusion-Related Reactions: Monitor patients for infusion-related reactions. Interrupt infusion for severe infusion reactions and institute appropriate medical management. (5.3)

6 ADVERSE REACTIONS

In patients with primary HLH, the most common adverse reactions (≥ 20%) were: infections, hypertension, infusion-related reactions, and pyrexia. (6.1)

In patients with HLH/MAS in Still’s disease, the most common adverse reactions (≥20%) were:viral infections, including cytomegalovirus infection or reactivation, and rash. (6.1)

To report SUSPECTED ADVERSE REACTIONS, contact 1-866-773-5274 or FDA at 1-800-FDA-1088 or www.fda.gov/medwatch.

FULL PRESCRIBING INFORMATION

1 INDICATIONS AND USAGE

GAMIFANT is indicated for the treatment of:

- adult and pediatric (newborn and older) patients with primary hemophagocytic lymphohistiocytosis (HLH) with refractory, recurrent or progressive disease or intolerance with conventional HLH therapy.
- adult and pediatric (newborn and older) patients with HLH/macrophage activation syndrome (MAS) in known or suspected Still’s disease, including systemic Juvenile Idiopathic Arthritis (sJIA), with an inadequate response or intolerance to glucocorticoids, or with recurrent MAS.

2 DOSAGE AND ADMINISTRATION

2.1 Recommended Dosage for Primary Hemophagocytic Lymphohistiocytosis

The recommended starting dose of GAMIFANT is 1 mg/kg given as a central or peripheral intravenous infusion over 1 hour twice per week (every three to four days). Doses subsequent to the initial dose may be increased based on clinical and laboratory criteria [see Dosage and Administration (2.5)].

Administer GAMIFANT until hematopoietic stem cell transplantation (HSCT) is performed or unacceptable toxicity. Discontinue GAMIFANT when a patient no longer requires therapy for the treatment of HLH.

2.2 Recommended Dosage for Hemophagocytic Lymphohistiocytosis/Macrophage Activation Syndrome

GAMIFANT is administered as a central or peripheral intravenous infusion over 1 hour according to the dosage schedule in Table 1. Doses may be increased based on clinical and laboratory criteria [see Dosage and Administration (2.6)]. Discontinue GAMIFANT when a patient no longer requires therapy for the treatment of HLH/MAS.

Table 1. GAMIFANT Dosage in Patients with HLH/MAS

Treatment Day | GAMIFANT Dosage
Day 1 | 6 mg/kg
Days 4 to 16 | 3 mg/kg every 3 days for 5 doses
From Day 19 onward | 3 mg/kg twice per week (i.e., every 3 to 4 days)

2.3 Monitoring to Assess Safety

Before Initiating GAMIFANT Treatment

Conduct testing for latent tuberculosis infections using the purified protein derivative (PPD) or IFNγ release assay and evaluate patients for tuberculosis risk factors prior to initiating GAMIFANT. Administer tuberculosis prophylaxis to patients at risk for tuberculosis, or known to have a positive PPD test result, or positive IFNγ release assay.

During GAMIFANT Treatment

Monitor for Herpes Zoster infection, adenovirus, EBV and CMV as clinically indicated.

2.4 Prophylaxis and Concomitant Medication Information

Prophylaxis

Consider prophylaxis for Herpes Zoster, Pneumocystis jirovecii, and for fungal infections prior to GAMIFANT administration.

Concomitant Medications

For primary HLH patients who are not receiving baseline dexamethasone treatment, begin dexamethasone at a daily dose of at least 5 mg/m^2 to 10 mg/m^2 the day before GAMIFANT treatment begins. For patients who were receiving baseline dexamethasone, they may continue their regular dose provided the dose is at least 5 mg/m2. Dexamethasone can be tapered according to the judgment of the treating physician [see Clinical Studies (14)].

2.5 Dose Modification Based on Response for Primary Hemophagocytic Lymphohistiocytosis

The GAMIFANT dose may be titrated up if disease response is unsatisfactory (see Table 2) [see Clinical Pharmacology (12.3)] . After the patient's clinical condition is stabilized, decrease the dose to the previous level to maintain clinical response.

Table 2: Dose Titration Criteria
Treatment Day | GAMIFANT Dose | Criteria for Dose Increase
Day 1 | Starting Dose of 1 mg/kg | N/A
From Day 4 onwards | Increase to 3 mg/kg | Unsatisfactory improvement in clinical condition, as assessed by a healthcare provider AND at least one of the following:; - Fever - persistence or recurrence - Platelet count - If baseline < 50,000/mm^3 and no improvement to > 50,000/mm^3 - If baseline > 50,000/mm^3 and less than 30% improvement - If baseline > 100,000/mm^3 and decrease to < 100,000/mm^3 - Neutrophil count - If baseline < 500/mm^3 and no improvement to > 500/mm^3 - If baseline > 500/mm^3 to 1,000/mm^3 and decrease to < 500/mm^3 - If baseline 1,000/mm^3 to 1,500/mm^3 and decrease to < 1,000/mm^3 - Ferritin (ng/mL) - If baseline ≥3,000 ng/mL and < 20% decrease - If baseline < 3,000 ng/mL and any increase to > 3,000 ng/mL - Splenomegaly - any worsening - Coagulopathy (both D-Dimer and Fibrinogen must apply) - D-Dimer - If abnormal at baseline and no improvement - Fibrinogen (mg/dL) - If baseline levels ≤100 mg/dL and no improvement - If baseline levels > 100 mg/dL and any decrease to < 100 mg/dL
From Day 7 onwards | Increase to 6 mg/kg | Unsatisfactory improvement in clinical condition, as assessed by a healthcare provider AND at least one of the following:; - Fever - persistence or recurrence - Platelet count - If baseline < 50,000/mm^3 and no improvement to > 50,000/mm^3 - If baseline > 50,000/mm^3 and less than 30% improvement - If baseline > 100,000/mm^3 and decrease to < 100,000/mm^3 - Neutrophil count - If baseline < 500/mm^3 and no improvement to > 500/mm^3 - If baseline > 500/mm^3 to 1,000/mm^3 and decrease to < 500/mm^3 - If baseline 1,000/mm^3 to 1,500/mm^3 and decrease to < 1,000/mm^3 - Ferritin (ng/mL) - If baseline ≥3,000 ng/mL and < 20% decrease - If baseline < 3,000 ng/mL and any increase to > 3,000 ng/mL - Splenomegaly - any worsening - Coagulopathy (both D-Dimer and Fibrinogen must apply) - D-Dimer - If abnormal at baseline and no improvement - Fibrinogen (mg/dL) - If baseline levels ≤100 mg/dL and no improvement - If baseline levels > 100 mg/dL and any decrease to < 100 mg/dL
From Day 10 onwards | Increase to 10 mg/kg | Assessment by a healthcare provider that based on initial signs of response, a further increase in GAMIFANT dose can be of benefit

2.6 Dose Modification Based on Response for Hemophagocytic Lymphohistiocytosis/Macrophage Activation Syndrome

Table 3: Dosage Adjustment Criteria

Treatment Day | GAMIFANT Dose | Dose Adjustments
Day 1 | Initial dose of 6 mg/kg | If unsatisfactory improvement in clinical condition, as assessed by a healthcare provider, the dose of GAMIFANT may be increased to:; - a maximum cumulative dose of 10 mg/kg over 3 days; AND the frequency may be increased to:; - every 2 days or once daily; After the patient’s clinical condition has improved, consider decreasing the dose to the previous level and assess whether clinical response is maintained.; If the clinical condition is not stabilized while receiving the maximum dosage, consider discontinuing GAMIFANT.
Days 4 to 16 | 3 mg/kg every 3 days for 5 doses | If unsatisfactory improvement in clinical condition, as assessed by a healthcare provider, the dose of GAMIFANT may be increased to:; - a maximum cumulative dose of 10 mg/kg over 3 days; AND the frequency may be increased to:; - every 2 days or once daily; After the patient’s clinical condition has improved, consider decreasing the dose to the previous level and assess whether clinical response is maintained.; If the clinical condition is not stabilized while receiving the maximum dosage, consider discontinuing GAMIFANT.
From Day 19 onwards | 3 mg/kg twice per week (i.e., every 3 to 4 days) | If unsatisfactory improvement in clinical condition, as assessed by a healthcare provider, the dose of GAMIFANT may be increased to:; - a maximum cumulative dose of 10 mg/kg over 3 days; AND the frequency may be increased to:; - every 2 days or once daily; After the patient’s clinical condition has improved, consider decreasing the dose to the previous level and assess whether clinical response is maintained.; If the clinical condition is not stabilized while receiving the maximum dosage, consider discontinuing GAMIFANT.

2.7 Instructions for Preparation and Administration

Preparation

GAMIFANT vials are for single dose only.

Do not mix GAMIFANT 5 mg/mL and 25 mg/mL vials together.

Prepare the solution for infusion as follows:

- Calculate the dose (mg/kg), total volume (mL) of GAMIFANT required and the number of GAMIFANT vials needed based on patient actual body weight [see Dosage and Administration (2.1)].

- Parenteral drug products should be inspected visually for particulate matter and discoloration prior to administration, whenever solution and container permit. GAMIFANT is a clear to slightly opalescent, colorless to slightly yellow liquid. Do not administer if discolored or foreign particulate matter is present.
- Withdraw the necessary amount of GAMIFANT solution and dilute with 0.9% Sodium Chloride Injection, USP.
  - For GAMIFANT 5 mg/mL vials:
    - Dilute to a maximum concentration of 2.5 mg/mL. Do not dilute product to less than 0.25 mg/mL.
    - The diluted solution can be placed in either a syringe or an infusion bag, depending on the volume needed.
    - When using a syringe, use a gamma irradiated or ethylene oxide sterilized latex-free, polyvinyl chloride (PVC)-free syringe.
    - When using an infusion bag, use a non-PVC polyolefin infusion bag.
  - For GAMIFANT 25 mg/mL vials:
    - Dilute to a maximum concentration of 12.5 mg/mL. Do not dilute product to less than 1.25 mg/mL.
    - Use a non-PVC polyolefin infusion bag made from either polyethylene or ethylene/propylene copolymer.
- Discard any unused portion left in the vial(s).

Administration

- Administer GAMIFANT diluted solution intravenously over 1 hour through a central or peripheral intravenous line containing a sterile, non-pyrogenic, low-protein binding 0.2 micron in-line filter.
- Do not infuse GAMIFANT concomitantly with other agents and do not add any other product to the infusion bag or syringe.
- Do not store any unused portion of the infusion solution for reuse. Any unused product or waste material should be disposed of in accordance with local requirements.

Storage of Diluted Solution

This product does not contain a preservative.

If not administered immediately:

- Store the diluted solution of GAMIFANT under refrigeration at 2°C to 8°C (36°F to 46°F) for no more than 4 hours from the time of dilution.
- If refrigerated, allow the diluted solution to come to room temperature prior to administration.
- Do not freeze. Do not shake.

3 DOSAGE FORMS AND STRENGTHS

GAMIFANT is a clear to slightly opalescent, colorless to slightly yellow preservative-free solution available as:

Injection:

• 10 mg/2 mL (5 mg/mL) in a single-dose vial

• 50 mg/10 mL (5 mg/mL) in a single-dose vial

• 100 mg/20 mL (5 mg/mL) in a single-dose vial

• 50 mg/2 mL (25 mg/mL) in a single-dose vial

• 100 mg/4 mL (25 mg/mL) in a single-dose vial

• 250 mg/10 mL (25 mg/mL) in a single-dose vial

• 500 mg/20 mL (25 mg/mL) in a single-dose vial

4 CONTRAINDICATIONS

None.

5 WARNINGS AND PRECAUTIONS

5.1 Infections

GAMIFANT may increase the risk of fatal and serious infections to include specific pathogens favored by IFNγ neutralization, including mycobacteria, Herpes Zoster virus, and Histoplasma Capsulatum.

Do not administer GAMIFANT in patients with infections caused by these pathogens until appropriate treatment has been initiated.

In patients with primary HLH receiving GAMIFANT in clinical trials, serious infections such as sepsis, pneumonia, bacteremia, disseminated histoplasmosis, necrotizing fasciitis, viral infections, and perforated appendicitis were observed in 32% of patients. The reported infections were viral (41%), bacterial (35%), fungal (9%), and the pathogen was not identified in 15% of cases.

In patients with HLH/MAS in Still’s disease receiving GAMIFANT in clinical trials, serious infections such as pneumonia, cytomegalovirus infection, cytomegalovirus infection reactivation, and sepsis were observed in 13% of patients. The reported infections were viral (44%), bacterial (13%), fungal (3%) and the pathogen was not identified in (13%) of patients.

Evaluate patients for tuberculosis risk factors and test for latent infection (PPD testing, PCR, or IFNγ release assay) prior to initiating GAMIFANT. Administer tuberculosis prophylaxis to patients at risk for tuberculosis or known to have a positive purified protein derivative (PPD) test result [see Dosage and Administration (2.2)].

Consider prophylaxis for Herpes Zoster, Pneumocystis jirovecii, and fungal infection to mitigate the risk to patients while receiving GAMIFANT [see Dosage and Administration (2.3)]. Employ surveillance testing during treatment with GAMIFANT.

Closely monitor patients receiving GAMIFANT for signs or symptoms of infection, promptly initiate a complete diagnostic workup appropriate for an immunocompromised patient, and initiate appropriate antimicrobial therapy.

5.2 Increased Risk of Infection with Use of Live Vaccines

Do not administer live or live attenuated vaccines to patients receiving GAMIFANT and for at least 4 weeks after the last dose of GAMIFANT. The safety of immunization with live vaccines during or following GAMIFANT therapy has not been studied.

5.3 Infusion-Related Reactions

Infusion-related reactions in patients with primary HLH, including drug eruption, pyrexia, rash, erythema, and hyperhidrosis, were reported with GAMIFANT treatment in 27% of patients. In one-third of these patients, the infusion-related reaction occurred during the first infusion.

Infusion-related reactions in patients with HLH/MAS in Still’s disease, including pyrexia, headache, paresthesia, bone pain, pruritic rash, and peripheral coldness, were reported with GAMIFANT treatment in 13% of patients. Infusion related reactions were reported as mild in 8% of patients and as moderate in 5% of patients.

Monitor patients for infusion-related reactions which can be severe. Interrupt the infusion for infusion reactions and institute appropriate medical management prior to continuing infusion at a slower rate.

6 ADVERSE REACTIONS

The following adverse reactions are described elsewhere in the labeling:

- Infections [see Warnings and Precautions (5.1)]
- Increased Risk of Infection with Use of Live Vaccines [see Warnings and Precautions (5.2)]
- Infusion-Related Reactions [see Warnings and Precautions (5.3)]

6.1 Clinical Trial Experience

Because clinical trials are conducted under widely varying conditions, adverse reaction rates observed in the clinical trials of a drug cannot be directly compared to rates in the clinical trials of another drug and may not reflect the rates observed in practice.

Primary HLH

The safety data described in this section reflect exposure to GAMIFANT in which 34 patients with untreated primary HLH and previously treated patients with primary HLH (NCT01818492) received GAMIFANT at a starting dose of 1 mg/kg every 3 days with dose increases up to 10 mg/kg [see Dosage and Administration (2.1) and Clinical Studies (14)]. The median duration of treatment with GAMIFANT was 59 days (range: 4 to 245 days) and the median cumulative dose was 25 mg/kg (range: 4 to 254 mg/kg).

The median age of study population was 1 year (range: 0.1 to 13 years), 53% were female, and 65% were Caucasian.

Serious adverse reactions were reported in 53% of patients. The most common serious adverse reactions (≥3%) included infections, gastrointestinal hemorrhage, and multiple organ dysfunction. Fatal adverse reactions occurred in two (6%) of patients and included septic shock and gastrointestinal hemorrhage.

Disseminated histoplasmosis led to drug discontinuation in one patient. The most commonly reported adverse reactions (≥20%) were infections, hypertension, infusion-related reactions, and pyrexia. Adverse reactions reported in ≥10% of patients during treatment with GAMIFANT are presented in Table 4.

Table 4: Adverse Reactions Reported in 10% of Patients with Primary HLH

Adverse Reactions | GAMIFANT; (%); (N = 34)
Infectionsa | 56
Hypertensionb | 41
Infusion-related reactionsc | 27
Pyrexia | 24
Hypokalemia | 15
Constipation | 15
Rash | 12
Abdominal pain | 12
Cytomegalovirus infection | 12
Diarrhea | 12
Lymphocytosis | 12
Cough | 12
Irritability | 12
Tachycardia | 12
Tachypnea | 12

aIncludes viral, bacterial, fungal, and infections in which no pathogen was identified

bIncludes secondary hypertension

cIncludes events of drug eruption, pyrexia, rash, erythema, and hyperhidrosis

Additional selected adverse reactions (all grades) that were reported in less than 10% of patients treated with GAMIFANT included: vomiting, acute kidney injury, asthenia, bradycardia, dyspnea, gastro-intestinal hemorrhage, epistaxis, and peripheral edema.

HLH/MAS

The safety of GAMIFANT was evaluated in two open-label clinical studies in patients with HLH/MAS in Stills disease, including sJIA [see Clinical Studies (14.2)].

The pooled safety data from these two studies included 39 patients who received an initial dose of 6 mg/kg followed by 3 mg/kg every 3 days until Day 16, and then twice weekly thereafter. The median duration of treatment with GAMIFANT was 29 days (range: 7 to 220 days) and the median cumulative dose was 33 mg/kg (range: 12 to 175 mg/kg).

Serious adverse reactions were reported in 12 patients (31%), with the most common serious adverse reaction being pneumonia (5%). Fatal adverse reactions occurred in two patients (5%) and included multiple organ dysfunction and circulatory shock.

Pneumonia led to drug discontinuation in one patient (3%). The most common adverse reactions (≥20%) were viral infections, including cytomegalovirus infection or reactivation, and rash. Adverse reactions reported in ≥ 10% of patients in the pooled safety analysis up to Week 8 during treatment with GAMIFANT are presented in Table 5.

Table 5: Adverse Reactions Reported in ≥10% of Patients with HLH/MAS in Stills disease

Adverse Reactions | GAMIFANT; (%); (N = 39)
Viral infectiona; Cytomegalovirus infection or reactivation | 44; 36
Rashb | 21
Anemiac | 18
Leukopeniad | 15
Thrombosis | 15
Bacterial infection | 13
Headache | 13
Hyperglycemia | 13
Infusion-related reactionse | 13
Abdominal pain | 10
Hypertension | 10
Pyrexia | 10
Thrombocytopenia | 10

aIncludes: Cytomegalovirus infection reactivation, Cytomegalovirus infection, Adenovirus test positive, Cytomegalovirus test positive, BK polyomavirus test positive, Respirovirus test positive, Parainfluenzae virus infection, COVID-19, Rhinovirus infection, gastroenteritis Rotavirus, Adenovirus infection, Human herpesvirus 6 infection reactivation, Adenovirus reactivation

bIncludes: rash maculo-papular, rash erythematous, rash pruritic, urticaria

cIncludes: anemia macrocytic, and hypochromic anemia

dIncludes: granulocytopenia, neutropenia

eInfusion-related reactions were defined as any event reported to have occurred within 24 hours after the start of infusion and assessed as related to study treatment

7 DRUG INTERACTIONS

7.1 Effect of GAMIFANT on Cytochrome P450 Substrates

The formation of CYP450 enzymes may be suppressed by increased levels of cytokines (such as IFNγ) during chronic inflammation. By neutralizing IFNγ, use of GAMIFANT may normalize CYP450 activities which may reduce the efficacy of drugs that are CYP450 substrates due to increased metabolism.

Upon initiation or discontinuation of concomitant GAMIFANT, monitor for reduced efficacy and adjust dosage of CYP450 substrate drugs as appropriate.

8 USE IN SPECIFIC POPULATIONS

8.1 Pregnancy

Risk Summary

There are no available data on GAMIFANT use in pregnant women to inform a drug-associated risk of adverse developmental outcomes. In an animal reproduction study, a murine surrogate anti-mouse IFNγ antibody administered to pregnant mice throughout gestation crossed the placental barrier, and no fetal harm was observed (see Data) .

The estimated background risk of major birth defects and miscarriage for the indicated population is unknown. All pregnancies have a background risk of birth defect, loss, or other adverse outcomes. In the U.S. general population, the estimated background risk of major birth defects and miscarriage in clinically recognized pregnancies is 2 to 4% and 15 to 20%, respectively.

Data

Animal Data

In a mouse embryo-fetal development study, a murine surrogate anti-mouse IFNγ antibody was administered every 3-4 days throughout organogenesis and late gestation at doses of 0, 30, 75 or 150 mg/kg/occasion. The surrogate antibody was detected in the plasma of all treated pregnant mice and their corresponding fetuses. No maternal toxicity occurred and there was no evidence of teratogenicity or effects on embryo-fetal survival or growth.

8.2 Lactation

Risk Summary

There is no information regarding the presence of emapalumab-lzsg in human milk, the effects on the breastfed child, or the effects on milk production. Published data suggest that only limited amounts of therapeutic antibodies are found in breast milk and they do not enter the neonatal and infant circulations in substantial amounts.

The developmental and health benefits of breastfeeding should be considered along with the mother's clinical need for GAMIFANT and any potential adverse effects on the breastfed child from GAMIFANT or from the underlying maternal condition.

8.4 Pediatric Use

Safety and effectiveness of GAMIFANT have been established in pediatric patients, newborn and older, with primary HLH that is reactivated or refractory to conventional therapies and with HLH/MAS in Still’s Disease (including sJIA) with an inadequate response to glucocorticoids [see Clinical Studies (14)]. Use of GAMIFANT is supported by 3 single-arm trials which included 57 pediatric patients: 27 with primary HLH and 30 with HLH/MAS in Still’s disease. These studies included pediatric patients in the following age groups: 5 patients newborn to 6 months, 13 patients 6 months to 2 years, 27 patients from 2 years to <12 years, and 12 patients from 12 years to <17 years.

8.5 Geriatric Use

Clinical studies of GAMIFANT did not include sufficient numbers of subjects aged 65 and over to determine whether they respond differently from younger subjects. Other reported clinical experience has not identified differences in responses between the elderly and younger patients.

10 OVERDOSAGE

Consider contacting the Poison Help line (1-800-222-1222) or a medical toxicologist for additional overdose management recommendations.

11 DESCRIPTION

Emapalumab-lzsg is an interferon gamma (IFNγ) neutralizing antibody. Emapalumab-lzsg is produced in Chinese Hamster Ovary cells by recombinant DNA technology. Emapalumab-lzsg is an IgG1 immunoglobulin with a molecular weight of approximately 148 kDa.

GAMIFANT (emapalumab-lzsg) injection for intravenous use is a sterile, preservative-free, clear to slightly opalescent, colorless to slightly yellow solution provided in single-dose vials that require dilution prior to intravenous infusion.

GAMIFANT 5 mg/mL (2 mL, 10 mL and 20 mL)

Each vial contains 10 mg/2 mL, 50 mg/10 mL, or 100 mg/20 mL emapalumab-lzsg at a concentration of 5 mg/mL. Each mL also contains the following inactive ingredients: L-Histidine (1.55 mg), L-Histidine monohydrochloride, monohydrate (3.14 mg), Polysorbate 80 (0.05 mg), sodium chloride (7.30 mg), and Water for Injection, USP.

GAMIFANT 25 mg/mL (2 mL, 4 mL, 10 mL and 20 mL)

Each vial contains 50 mg/2 mL, 100 mg/4 mL, 250 mg/10 mL or 500 mg/20 mL emapalumab- lzsg at a concentration of 25 mg/mL. Each mL also contains the following inactive ingredients: L-Histidine (1.55 mg), L-Histidine monohydrochloride, monohydrate (3.14 mg), Polysorbate 80 (0.05 mg), sodium chloride (7.30 mg), and Water for Injection, USP.

12 CLINICAL PHARMACOLOGY

12.1 Mechanism of Action

Emapalumab-lzsg is a monoclonal antibody that binds to and neutralizes interferon gamma (IFNγ). Nonclinical data suggest that IFNγ plays a pivotal role in the pathogenesis of HLH by being hypersecreted.

12.2 Pharmacodynamics

IFNγ Inhibition

Emapalumab-lzsg reduces the plasma concentrations of CXCL9, a chemokine induced by IFNγ.

Cardiac Electrophysiology

At a dose of 3 mg/kg GAMIFANT does not prolong the QT interval to any clinically relevant extent.

12.3 Pharmacokinetics

The pharmacokinetics of emapalumab-lzsg were evaluated in healthy adult subjects and in patients with HLH.

Following a 1 mg/kg emapalumab-lzsg dose, median steady state peak concentration was 44 mcg/mL, which was 2.9 times higher than after the first dose. The median steady state trough concentration was 25 mcg/mL, which was 4.3 times higher than after the first dose.

Emapalumab-lzsg AUC increases slightly more than proportionally between 1 and 3 mg/kg doses, and less than proportionally at 3, 6, and 10 mg/kg doses.

Emapalumab-lzsg exhibits target-mediated-like clearance dependent on IFNγ production, which can vary between and within patients as a function of time and can affect the recommended dosage [see Dosage and Administration (2.2)] . Emapalumab-lzsg steady state is achieved by the 7th infusion when the IFNγ production is moderate. At high IFNγ production, steady-state is reached earlier due to a shorter half-life.

Distribution

The central and peripheral volumes of distribution in a subject with body weight of 70 kg are 2.8 and 4.4 L, respectively.

Elimination

Emapalumab-lzsg elimination half-life is approximately 22 days in healthy subjects and ranged from 2.5 to 18.9 days in HLH patients.

In patients with HLH, the elimination half-life of emapalumab-lzsg was significantly influenced by the amount of IFNγ within the patient, demonstrating a target mediated clearance-like mechanism. The elimination half-life of emapalumab-lzsg is reduced as the concentration of IFNγ increases.

Emapalumab-lzsg clearance is approximately 0.007 L/h in healthy subjects.

Metabolism

The metabolic pathway of emapalumab-lzsg has not been characterized. Like other protein therapeutics, GAMIFANT is expected to be degraded into small peptides and amino acids via catabolic pathways.

Specific Populations

Body weight (3 to 80 kg) was a significant covariate of emapalumab-lzsg pharmacokinetics, supporting body weight-based dosing.

No clinically significant differences in the pharmacokinetics of emapalumab-lzsg were observed based on age (0.02 to 64 year), sex (53% Females), race (71.4% Caucasian, 12.2% Asian and 8.2% Black), renal impairment including dialysis, or hepatic impairment (mild, moderate, and severe).

Drug Interaction Studies

No drug-drug interaction studies have been conducted with GAMIFANT.

12.4 Immunogenicity

As with all therapeutic proteins, there is potential for immunogenicity. The detection of antibody formation is highly dependent on the sensitivity and specificity of the assay. Additionally, the observed incidence of antibody (including neutralizing antibody) positivity in an assay may be influenced by several factors, including assay methodology, sample handling, timing of sample collection, concomitant medications, and underlying disease. For these reasons, comparison of the incidence of antibodies in the studies described below with the incidence of antibodies in other studies or to other emapalumab products may be misleading.

The immunogenicity of emapalumab-lzsg has been evaluated using an electrochemiluminescence-based immunoassay (ECLIA).Treatment-emergent anti-drug antibodies (ADAs) were detected in 1/33 (3%) of patients in the primary HLH clinical trial. The ADAs in this patient were found to have neutralizing ability. Treatment-emergent ADAs were detected in 5/35 patients (14%) in the two HLH/MAS clinical trials. None of the ADAs in these 5 patients were found to have neutralizing ability. No evidence of an altered pharmacokinetic, safety or efficacy profile was identified in primary HLH or HLH/MAS patients who developed antibodies to emapalumab-lzsg.

13 NONCLINICAL TOXICOLOGY

13.1 Carcinogenesis, Mutagenesis, Impairment of Fertility

No carcinogenicity or genotoxicity studies have been conducted with emapalumab-lzsg.

No studies have been conducted to evaluate the effects of emapalumab-lzsg on fertility; however, no adverse effects on male or female reproductive organs were observed in the 8- or 13-week repeat-dose toxicity studies in cynomolgus monkeys.

14 CLINICAL STUDIES

14.1 Primary Hemophagocytic Lymphohistiocytosis

The efficacy of GAMIFANT was evaluated in a multicenter, open-label, single-arm trial NI-0501-04 (NCT01818492) in 27 pediatric patients with suspected or confirmed primary Hemophagocytic lymphohistiocytosis (HLH) with either refractory, recurrent, or progressive disease during conventional HLH therapy or who were intolerant of conventional HLH therapy.

Patients were required to fulfill the following criteria for enrollment: primary HLH based on a molecular diagnosis or family history consistent with primary HLH or five out of the 8 criteria fulfilled: fever, splenomegaly, cytopenias affecting 2 of 3 lineages in the peripheral blood (hemoglobin < 9, platelets < 100 x 10^9/L, neutrophils < 1 x 10^9/L), hypertriglyceridemia (fasting triglycerides > 3 mmol/L or ≥265 mg/dL) and/or hypofibrinogenemia (≤1.5 g/L), hemophagocytosis in bone marrow, spleen, or lymph nodes with no evidence of malignancy, low or absent NK-cell activity, ferritin ≥500 mcg/L, soluble CD25 ≥2400 U/mL. Patients had to have evidence of active disease as assessed by the treating physician. Patients had to fulfill one of the following criteria as assessed by the treating physician: having not responded or not achieved a satisfactory response or not maintained a satisfactory response to conventional HLH therapy, or intolerance to conventional HLH treatments. Patients with active infections caused by specific pathogens favored by IFNγ neutralization were excluded from the trial (e.g., mycobacteria and Histoplasma Capsulatum). Patients received prophylaxis for Herpes Zoster, Pneumocystis jirovecii, and fungal infections.

Twenty-seven patients enrolled and received treatment in the study and twenty patients (74%) completed the study. Seven patients (26%) were prematurely withdrawn. Twenty-two patients (81%) enrolled onto the open-label extension study which monitored patients for up to 1 year after HSCT or after the last GAMIFANT infusion (NI-0501-05; NCT02069899).

The study treatment duration was up to 8 weeks after which patients could continue treatment on the extension study. All patients received an initial starting dose of GAMIFANT of 1 mg/kg every 3 days. Subsequent doses could be increased to a maximum of 10 mg/kg based on clinical and laboratory parameters interpreted as unsatisfactory response. Forty-four percent of patients remained at a dose of 1 mg/kg, 30% of patients increased to 3-4 mg/kg and 26% of patients increased to 6-10 mg/kg. The median time to dose increase was 27 days (range: 3-31 days) with 22% of patients requiring a dose increase in the first week of treatment.

All patients received dexamethasone as background HLH treatment with doses between 5 to 10 mg/m^2/day. Cyclosporine A was continued if administered prior to screening. Patients receiving methotrexate and glucocorticoids administered intrathecally at baseline could continue these treatments.

In Study NI-0501-04, the median patient age was 1 year (0.2 to 13). Fifty-nine percent of the patients were female, 63% were Caucasian, 11% were Asian, and 11% were Black.

A genetic mutation known to cause HLH was present in 82% of patients. The most frequent causative mutations were FHL3-UNC13D (MUNC 13-4) (26%), FHL2-PRF1 (19%), and Griscelli Syndrome type 2 (19%).

The HLH mutations in the population enrolled are described in Table 6

Table 6: HLH Mutations in Patients with Primary HLH with Prior Therapy
 | GAMIFANT (N=27)
HLH Genetic Confirmation | 22 (82)
FHL3 UNC13D | 7 (26)
FHL2 PRF1 | 5 (19)
Griscelli Syndrome type 2 (RAB27A) | 5 (19)
FHL5 STXBP2 (UNC18B) | 2 (7.4)
FHL4 STX11 | 1 (3.7)
X-linked Lymphoproliferative Disorder 1 | 1 (3.7)
X-linked Lymphoproliferative Disorder 2 | 1 (3.7)

All patients received previous HLH treatments. Patients received a median of 3 prior agents before enrollment into the trial. Prior regimens included combinations of the following agents: dexamethasone, etoposide, cyclosporine A, and anti-thymocyte globulin.

At baseline entry into the study, 78% of patients had elevated ferritin levels, thrombocytopenia (70% with platelet count of < 100 x 10^9cells/L), hypertriglyceridemia (67%) with triglyceride level >3 mmol/L. Central nervous system findings were present in 37% of patients. Forty-one percent of patients had active infections not due to specific pathogens favored by IFNγ neutralization at the time of GAMIFANT initiation.

The efficacy of GAMIFANT was based upon overall response rate (ORR) at the end of treatment, defined as achievement of either a complete or partial response or HLH improvement. ORR was evaluated using an algorithm that included the following objective clinical and laboratory parameters: fever, splenomegaly, central nervous system symptoms, complete blood count, fibrinogen and/or D-dimer, ferritin, and soluble CD25 (also referred to as soluble interleukin-2 receptor) levels. Complete response was defined as normalization of all HLH abnormalities (i.e., no fever, no splenomegaly, neutrophils >1x10^9/L, platelets >100x10^9/L, ferritin <2,000 µg/L, fibrinogen >1.50 g/L, D-dimer <500 µg/L, normal CNS symptoms, no worsening of sCD25 >2-fold baseline). Partial response was defined as normalization of ≥3 HLH abnormalities. HLH improvement was defined as ≥3 HLH abnormalities improved by at least 50% from baseline.

Table 7: Overall Response Rate at End of Treatment
 | GAMIFANT (N=27)
Overall Response Rate
N (%) | 17 (63)
(95% CI) | (0.42, 0.81)
p-value† | 0.013
Overall Response by Category
Complete response, n (%) | 7 (26)
Partial response | 8 (30)
HLH improvement | 2 (7.4)

†p-value based on Exact Binomial Test at a one-sided significance level of 2.5% comparing proportion of patients with overall response to hypothesized null hypothesis of 40%.
CI = confidence interval

The median duration of first response, defined as time from achievement of first response to loss of first response, is not reached (range: 4-56+ days). Seventy percent (19/27) of patients proceeded to HSCT.

14.2 Hemophagocytic Lymphohistiocytosis/Macrophage Activation Syndrome in Still’s disease

The efficacy of GAMIFANT was evaluated in two open-label, single arm, multicenter studies which enrolled a total of 39 patients with hemophagocytic lymphohistiocytosis (HLH)/macrophage activation syndrome (MAS) in Still’s disease, including systemic Juvenile Idiopathic Arthritis (sJIA), with an inadequate response to high-dose glucocorticoid treatment.

In each study, patients were required to fulfill the following criteria for enrollment: confirmed or suspected diagnosis of sJIA or AOSD; a diagnosis of active MAS with ferritin >684 ng/mL and any 2 of these 4 laboratory criteria: platelet count ≤181×10^9/L, AST >48 U/L, triglycerides >156 mg/dL, or fibrinogen levels ≤360 mg/dL; an inadequate response to high-dose IV glucocorticoids. Patients with active infections caused by specific pathogens favored by IFNγ neutralization were excluded from the trial (e.g., mycobacteria and Histoplasma Capsulatum).

In each study, GAMIFANT was administered at an initial dose of 6 mg/kg, followed by at least 3 mg/kg every 3 days until Day 16, and then twice weekly thereafter. Glucocorticoids and anakinra (<4 mg/kg/d) could be co-administered for the treatment of Still’s disease.

Pooled Data

The pooled analysis includes all patients from Study NI-0501-06 (NCT03311854) and Study NI-0501-14 (NCT05001737). These two studies enrolled 39 patients who received GAMIFANT, and 37 patients completed the studies (95%). The majority of patients were female (80%) and the median age was 12.0 years (range: 0.9 to 64 years). The racial distribution was White (74%), Asian (10%), Black or African American (5%), and Other (3%), with 3 patients not reporting race (8%). Ethnicity was only collected in Study NI-0501-14 in which 88% reported Not Hispanic or Latino with 3 patients not reporting ethnicity (12%). At baseline, patients had elevated ferritin levels (median 6833 µg/L), elevated ALT (median 259 U/L), and elevated LDH (median 954 U/L).

The efficacy of GAMIFANT was based on complete response (CR), a composite endpoint consisting of clinical resolution of MAS signs and symptoms (a visual analogue scale (VAS), of ≤1 cm [range 0 to 10 cm]) and the following 7 laboratory parameter endpoints: WBC count and platelet count above the lower limit of normal (LLN), LDH, AST and ALT below 1.5×the upper limit of normal (ULN), fibrinogen >100 mg/dL, and ferritin levels decreased ≥80% from values at screening or baseline (whichever was higher) or <2000 ng/mL, whichever was lower (see Table 8).

Table 8 – Pooled Efficacy Results

Composite endpoint and individual components at Week 8 | n/N | % of patients | 95% CIa
Complete response (CR) | 21/39 | 53.8 | 37.2, 69.9
Clinical MAS remission (VAS ≤ 1 cm)b | 32/39 | 82.1 | 66.5, 92.5
Ferritin reduction to < 2000 ng/mL or an 80% decreasec | 33/39 | 84.6 | 69.5, 94.1
Platelet count above the LLN | 34/39 | 87.2 | 72.6, 95.7
ALT below 1.5× ULN | 34/39 | 87.2 | 72.6, 95.7
AST below 1.5×ULN | 37/39 | 94.9 | 82.7, 99.4
Fibrinogen > 100 mg/dL | 35/39 | 89.7 | 75.8, 97.1
WBC above the LLN | 36/39 | 92.3 | 79.1, 98.4
LDH below 1.5×ULN | 26/39 | 66.7 | 49.8, 80.9

aClopper-Pearson confidence interval is presented: two-sided 95% confidence interval

bClinical MAS remission was assessed using a visual analogue scale (VAS) where 0 cm referred to no clinical signs or symptoms of MAS and 10 cm referred to the worst possible clinical signs and symptoms of MAS

c80% decrease calculated from values at screening or baseline (whichever was highest) or < 2000 ng/mL, whichever was lowest

16 HOW SUPPLIED/STORAGE AND HANDLING

GAMIFANT (emapalumab-lzsg) injection is a sterile, clear to slightly opalescent, colorless to slightly yellow solution supplied in the following packaging configuration:

NDC 66658-501-01 – containing one 10 mg/2 mL (5 mg/mL) single-dose vial

NDC 66658-505-01 – containing one 50 mg/10 mL (5 mg/mL) single-dose vial

NDC 66658-510-01 – containing one 100 mg/20 mL (5 mg/mL) single-dose vial

NDC 66658-522-01 – containing one 50 mg/2 mL (25 mg/mL) single-dose vial

NDC 66658-523-01 – containing one 100 mg/4 mL (25 mg/mL) single-dose vial

NDC 66658-524-01 – containing one 250 mg/10 mL (25 mg/mL) single-dose vial

NDC 66658-525-01 – containing one 500 mg/20 mL (25 mg/mL) single-dose vial

Store GAMIFANT in a refrigerator at 2ºC to 8ºC (36ºF to 46ºF) in original carton to protect from light. Do not freeze or shake. This product contains no preservative.

17 PATIENT COUNSELING INFORMATION

Advise the patient to read the FDA-approved patient labeling (Medication Guide).

Infections

Inform patients and their caregivers of the risk of developing infections during treatment with GAMIFANT, and to report any symptoms of infection [see Warnings and Precautions (5.1)] .

Vaccinations

Advise patients and their caregivers that the patient should not receive live or live attenuated vaccines during GAMIFANT treatment [see Warnings and Precautions (5.2)] .

Infusion-Related Reactions

Advise patients and their caregivers of the potential for developing infusion-related reactions during treatment with GAMIFANT [see Warnings and Precautions (5.3)].

Manufactured by:

Swedish Orphan Biovitrum AB (publ)
Stockholm, Sweden
U.S. License Number 1859

Distributed by:

Sobi Inc.
77 Fourth Avenue, 3 rdFloor
Waltham, MA 02451-7559

Manufactured at:

Patheon Italia S.p.A
2° Trav. SX Via Morolense, 5
03013-Ferentino Italy

Product of the United Kingdom

MEDICATION GUIDE
GAMIFANT ®(gam' i fant)
(emapalumab-lzsg)
injection, for intravenous use

What is the most important information I should know about GAMIFANT?
GAMIFANT can cause serious side effects including:
Infections. GAMIFANT is a medicine that affects your immune system and may lower the ability of your immune system to fight infections. GAMIFANT may increase your risk of serious infections that can lead to death. These infections include tuberculosis (TB), histoplasmosis, Herpes zoster infection (shingles) and other infections caused by viruses, fungi or bacteria that can spread throughout the body.
Your healthcare provider will:

- test you for TB before you start treatment with GAMIFANT.
- treat you with a medicine for TB if you at risk for TB or if you have a known positive TB test.

Infections are common in people treated with GAMIFANT.
Before starting GAMIFANT, tell your healthcare provider if you:

- had TB in the past, or if you or a member of your family have been in recent close contact with someone with TB.
- have ever had a positive TB skin test (PPD).
- currently have or have had history of infections, including histoplasmosis or Herpes zoster (shingles).
- are being treated for an active infection.
- have symptoms of an infection, such as fever, sweat and chills, cough, breathing problems, blood in mucus (phlegm), warm, red, or painful skin or sores on your body.

Your healthcare provider may give you medicine to help prevent certain infections before you receive GAMIFANT. After starting GAMIFANT, tell your healthcare provider if:

- new symptoms of an infection appear.
- symptoms of an infection that you already had when starting GAMIFANT worsen.

Your healthcare provider will monitor you closely for signs and symptoms of infections during treatment with GAMIFANT.
See " What are the possible side effects of GAMIFANT?" for more information about side effects.

What is GAMIFANT?
GAMIFANT is a prescription medicine used for the treatment of hemophagocytic lymphohistiocytosis (HLH) in adults and children (newborn and older) with:

- primary HLH whose disease has come back or progressed, or other medicines have not worked well enough or cannot be tolerated.
- HLH/macrophage activation syndrome (MAS) in known or suspected Stills disease, including systemic Juvenile Idiopathic Arthritis (sJIA), when glucocorticoids have not worked well enough or cannot be tolerated, or with MAS that has come back.

Before you receive GAMIFANT, tell your healthcare provider about all of your medical conditions including if you:

- have an infection (see What is the most important information I should know about GAMIFANT?)
- have received or are scheduled to receive an immunization (vaccine). You should not receive live or live attenuated vaccines during your treatment with GAMIFANT and for at least 4 weeks after the last dose of GAMIFANT.
- are pregnant or plan to become pregnant. It is not known if GAMIFANT can harm your unborn baby.
- are breastfeeding or plan to breastfeed. It is not known if GAMIFANT passes into your breast milk. Talk to your healthcare provider about the best way to feed your baby during treatment with GAMIFANT.

Tell your healthcare provider about all the medicines you take, including prescription and over-the-counter medicines, vitamins, and herbal supplements.

How will I receive GAMIFANT?

- You will receive GAMIFANT through a vein by intravenous (IV) infusion over 1 hour.
- Your healthcare provider will monitor you during the infusion for side effects.
- For primary HLH:

o GAMIFANT is given 2 times a week (every 3 to 4 days).
o GAMIFANT is used with another prescription medicine called dexamethasone. You can ask your healthcare provider for information about dexamethasone.

- For HLH/MAS in Stills disease, after your first dose, GAMIFANT is given every 3 days for 5 doses, then 2 times a week.
- Your healthcare provider will do blood tests during your treatment with GAMIFANT to see how well you respond to treatment.

What are the possible side effects of GAMIFANT?
GAMIFANT can cause serious side effects, including:
See What is the most important information I should know about GAMIFANT?
Infusion reactions. Infusion reactions are common with GAMIFANT, and can also be severe. Infusion reactions can happen during or shortly after treatment with GAMIFANT. Your healthcare provider may temporarily stop your infusion and treat your symptoms before continuing your infusion if you have severe infusion reactions. Tell your healthcare provider right away if you get any of the following symptoms:

o skin redness

o itching
o fever
o rash
o excessive sweating
o headache
o bone pain

o chills

o chest pain

o shortness of breath

o nausea or vomiting

o lightheadedness or dizziness

o tingling, burning, or numbness

o cold hands, arms, legs or feet

The most common side effects of GAMIFANT in people with primary HLH include: infections, high blood pressure (hypertension) and fever.
The most common side effects of GAMIFANT in people with HLH/MAS in Stills disease include: viral infection and rash.
These are not all the possible side effects of GAMIFANT.
Call your doctor for medical advice about side effects. You may report side effects to FDA at 1-800-FDA-1088.

General information about the safe and effective use of GAMIFANT.
Medicines are sometimes prescribed for purposes other than those listed in a Medication Guide. You can ask your healthcare provider or pharmacist for information about GAMIFANT that is written for health professionals.

What are the ingredients in GAMIFANT?
Active ingredient: emapalumab-lzsg
Inactive ingredients: L-Histidine, L-Histidine monohydrochloride, monohydrate, Polysorbate 80, sodium chloride, and Water for Injection
Manufactured by: Swedish Orphan Biovitrum AB (publ), Stockholm, Sweden, U.S. License Number 1859
Distributed by: Sobi Inc., 77 Fourth Avenue, 3rd Floor, Waltham, MA 02451-7559
Manufactured at: Patheon Italia S.p.A. 2° Trav. SX Via Morolense, 5, 03013-Ferentino Italy
Product of the United Kingdom
For more information call 1-866-773-5274 or go to www.gamifant.com

This Medication Guide has been approved by the U.S. Food and Drug Administration.

Revised: 06/2025

PACKAGE LABEL

Principal Display Panel - 10 mg/2 mL Carton Label

NDC 66658-501-01

Gamifant®
(emapalumab-lzsg)
Injection

10 mg/2 mL
(5 mg/mL)

For intravenous infusion only.

Requires dilution prior to administration.

Single-dose vial. Discard unused portion.

Rx only

Dispense the enclosed Medication Guide to each patient.

PACKAGE LABEL

Principal Display Panel - 50 mg/10 mL Carton Label

NDC 66658-505-01

Gamifant®
(emapalumab-lzsg)
Injection

50 mg/10 mL
(5 mg/mL)

For intravenous infusion only.

Requires dilution prior to administration.

Single-dose vial. Discard unused portion.

Rx only

Dispense the enclosed Medication Guide
to each patient.

PACKAGE LABEL

Principal Display Panel - 100 mg/20 mL Carton Label

NDC 66658-510-01

Gamifant®
(emapalumab-lzsg)
Injection

100 mg/20 mL
(5 mg/mL)

For intravenous infusion only.

Requires dilution prior to administration.

Single-dose vial. Discard unused portion.

Rx only

Dispense the enclosed Medication Guide
to each patient.

PACKAGE LABEL

Principal Display Panel – 50 mg/2 mL Carton Label

NDC 66658-522-01

Gamifant®

(emapalumab-lzsg)
Injection

50 mg/2 mL
(25 mg/mL)

For intravenous infusion only.

Requires dilution prior to administration.

Single-dose vial. Discard unused portion.

Rx only

Dispense the enclosed Medication Guide
to each patient.

PACKAGE LABEL

Principal Display Panel – 100 mg/4 mL Carton Label

NDC 66658-523-01

Gamifant®

(emapalumab-lzsg)
Injection

100 mg/4 mL
(25 mg/mL)

For intravenous infusion only.

Requires dilution prior to administration.

Single-dose vial. Discard unused portion.

Rx only

Dispense the enclosed Medication Guide
to each patient.

PACKAGE LABEL

Principal Display Panel – 250 mg/10 mL Carton Label

NDC 66658-524-01

Gamifant®

(emapalumab-lzsg)
Injection

250 mg/10 mL
(25 mg/mL)

For intravenous infusion only.

Requires dilution prior to administration.

Single-dose vial. Discard unused portion.

Rx only

Dispense the enclosed Medication Guide
to each patient.

PACKAGE LABEL

Principal Display Panel – 500 mg/20 mL Carton Label

NDC 66658-525-01

Gamifant®

(emapalumab-lzsg)
Injection

500 mg/20 mL
(25 mg/mL)

For intravenous infusion only.

Requires dilution prior to administration.

Single-dose vial. Discard unused portion.

Rx only

Dispense the enclosed Medication Guide
to each patient.